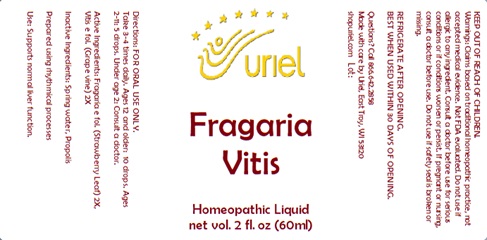 DRUG LABEL: Fragaria Vitis
NDC: 48951-4169 | Form: LIQUID
Manufacturer: Uriel Pharmacy Inc
Category: homeopathic | Type: HUMAN OTC DRUG LABEL
Date: 20240903

ACTIVE INGREDIENTS: VITIS VINIFERA LEAF 2 [hp_X]/1 mL; FRAGARIA VESCA WHOLE 2 [hp_X]/1 mL
INACTIVE INGREDIENTS: PROPOLIS WAX; WATER

Fragaria Vitis

INDICATIONS AND USAGE

Directions: FOR ORAL USE ONLY.

DOSAGE AND ADMINISTRATION

Take 3-4 times daily. Ages 12 and older: 10 drops. Ages 2-11: 5 drops. Under age 2: Consult a doctor.

ACTIVE INGREDIENT

Active Ingredients: Fragaria e fol. (Strawberry Leaf) 2X, Vitis e fol. (Grape vine) 2X

Inactive Ingredients: Distilled water, Propolis

Prepared using rhythmical processes.

PURPOSE

Use: Supports normal liver function.

KEEP OUT OF REACH OF CHILDREN.

WARNINGS

Warnings: Claims based on traditional homeopathic practice, not accepted medical evidence. Not FDA evaluated. Do not use if allergic to any ingredient. Consult a doctor before use for serious conditions or if conditions worsen or persist. If pregnant or nursing, consult a doctor before use. Do not use if safety seal is broken or missing.

REFRIGERATE AFTER OPENING.
BEST WHEN USED WITHIN 30 DAYS OF OPENING.

Questions? Call 866.642.2858
Made with care by Uriel, East Troy, WI 53120
shopuriel.com Lot: